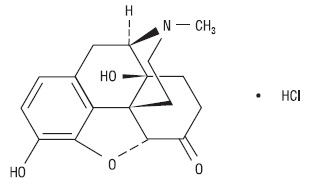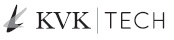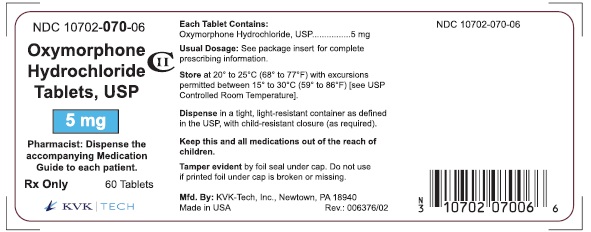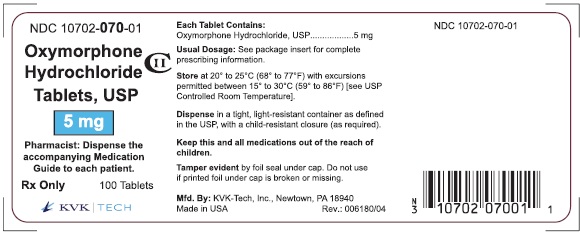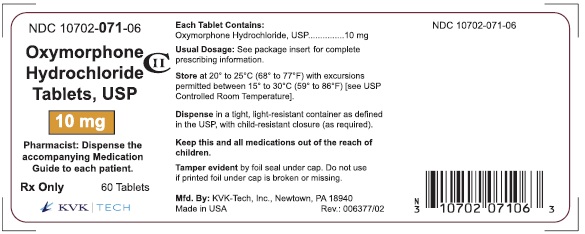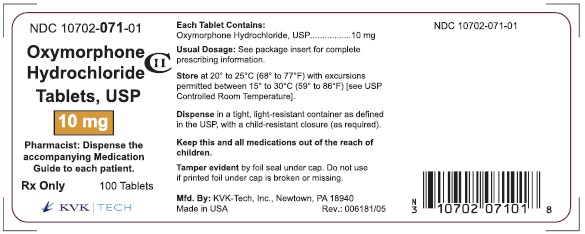 DRUG LABEL: Oxymorphone Hydrochloride
NDC: 10702-071 | Form: TABLET
Manufacturer: KVK-Tech, Inc.
Category: prescription | Type: HUMAN PRESCRIPTION DRUG LABEL
Date: 20260130
DEA Schedule: CII

ACTIVE INGREDIENTS: OXYMORPHONE HYDROCHLORIDE 10 mg/1 1
INACTIVE INGREDIENTS: LACTOSE MONOHYDRATE; MAGNESIUM STEARATE; STARCH, CORN; D&C RED NO. 30

HIGHLIGHTS OF PRESCRIBING INFORMATION

These highlights do not include all the information needed to use OXYMORPHONE HYDROCHLORIDE TABLETS safely and effectively. See full prescribing information for OXYMORPHONE HYDROCHLORIDE TABLETS.
OXYMORPHONE HYDROCHLORIDE tablets for oral use CII
Initial U.S. Approval: 1959

BOXED WARNING

WARNING: SERIOUS AND LIFE-THREATENING RISKS FROM USE OF OXYMORPHONE HYDROCHLORIDE TABLETS

See full prescribing information for complete boxed warning.

- Oxymorphone hydrochloride tablets exposes users to risks of addiction, abuse, and misuse, which can lead to overdose and death. Assess patient’s risk before prescribing and monitor regularly for these behaviors and conditions. (5.1)
- Serious, life-threatening, or fatal respiratory depression may occur. Monitor closely, especially upon initiation or following a dose increase. (5.2)
- Accidental ingestion of oxymorphone hydrochloride tablets, especially by children, can result in a fatal overdose of oxymorphone. (5.2)
- Concomitant use of opioids with benzodiazepines or other central nervous system (CNS) depressants, including alcohol, may result in profound sedation, respiratory depression, coma, and death. Reserve concomitant prescribing for use in patients for whom alternative treatment options are inadequate; limit dosages and durations to the minimum required; and follow patients for signs and symptoms of respiratory depression and sedation. (5.3, 7)
- Advise pregnant women using opioids for an extended period of time of the risk of Neonatal Opioid Withdrawal Syndrome, which may be life-threatening if not recognized and treated. Ensure that management by neonatology experts will be available at delivery. (5.4)
- To ensure that the benefits of opioid analgesics outweigh the risks of addiction, abuse, and misuse, the Food and Drug Administration (FDA) has required a Risk Evaluation and Mitigation Strategy (REMS) for these products. (5.5)
- Instruct patients not to consume alcohol or any product containing alcohol while taking oxymorphone hydrochloride tablets because co-ingestion can result in fatal plasma oxymorphone levels. (5.3)

RECENT MAJOR CHANGES

Boxed Warning 11/2025

Indications and Usage (1) 11/2025

Dosage and Administration (2.2, 2.9) 11/2025

Warnings and Precautions (5.1, 5.2, 5.3, 5.12, 5.14) 11/2025

1 INDICATIONS AND USAGE

Limitations of Use (1)

- Because of the risks of addiction, abuse, misuse, overdose, and death, which can occur at any dosage or duration and persist over the course of therapy, reserve opioid analgesics, including oxymorphone hydrochloride for use in patients for whom alternative treatment options are ineffective, not tolerated, or would be otherwise inadequate to provide sufficient management of pain. (1, 5.1)

2 DOSAGE AND ADMINISTRATION

- Oxymorphone hydrochloride tablets should be prescribed only by healthcare professionals who are knowledgeable about the use of opioids and how to mitigate the associated risks. (2.1)
- Use the lowest effective dosage for the shortest duration of time consistent with individual patient treatment goals. Reserve titration to higher doses of oxymorphone hydrochloride tablets for patients in whom lower doses are insufficiently effective and in whom the expected benefits of using a higher dose opioid clearly outweigh the substantial risks. (2.1, 5)
- Many acute pain conditions (e.g., the pain that occurs with a number of surgical procedures or acute musculoskeletal injuries) require no more than a few days of an opioid analgesic. Clinical guidelines on opioid prescribing for some acute pain conditions are available. (2.1)
- Initiate the dosing regimen for each patient individually, taking into account the patient’s underlying cause and severity of pain, prior analgesic treatment and response, and risk factors for addiction, abuse, and misuse. (2.1, 5.1)
- Respiratory depression can occur at any time during opioid therapy, especially when initiating and following dosage increases with oxymorphone hydrochloride tablets. Consider this risk when selecting an initial dose and when making dose adjustments. (2.1, 5.2)
- Initiate treatment with oxymorphone hydrochloride tablets in a dosing range of 10 mg to 20 mg every four to six hours as needed for pain, at the lowest dose necessary to achieve adequate analgesia. Titrate the dose based upon the individual patient’s response to their initial dose of Oxymorphone hydrochloride tablets. (2.8, 5)
- Oxymorphone hydrochloride tablets should be taken on an empty stomach, at least one hour prior to or two hours after eating. (2.1)
- Discuss opioid overdose reversal agents and options for acquiring them with the patient and/or caregiver, both when initiating and renewing treatment with oxymorphone hydrochloride tablets, especially if the patient has additional risk factors for overdose, or close contacts at risk for exposure and overdose. (2.2, 5.1, 5.2, 5.3)
- Conversion to oxymorphone hydrochloride tablets: Follow recommendations for conversion from other opioids or parenteral oxymorphone. (2.3)
- Mild Hepatic Impairment: Initiate treatment with 5 mg and titrate slowly. Monitor for signs of respiratory and central nervous system depression. (2.4)
- Renal Impairment: Initiate treatment with 5 mg and titrate slowly. Monitor for signs of respiratory and central nervous system depression. (2.5)
- Geriatric Patients: Initiate dosing with 5 mg, titrate slowly, and monitor for signs of respiratory and central nervous system depression. (2.6)
- CNS Depressants:Initiate treatment with 1/3 to 1/2 the recommended starting dose, consider using lower dosage of the concomitant CNS depressant, and monitor closely. (2.7, 5.7, 7)
- Periodically reassess patients receiving oxymorphone hydrochloride to evaluate the continued need for opioid analgesics to maintain pain control, for the signs or symptoms of adverse reactions, and for the development of addiction, abuse, or misuse. (2.8)
- Do not rapidly reduce or abruptly discontinue oxymorphone hydrochloride in a physically dependent patient because rapid dreduction or abrupt discontinuation of opioid analgesics has resulted in serious withdrawal symptoms, uncontrolled pain, and suicide. (2.9, 5.14)

3 DOSAGE FORMS AND STRENGTHS

Tablets: 5 mg and 10 mg. (3)

4 CONTRAINDICATIONS

- Significant respiratory depression. (4)
- Acute or severe bronchial asthma in an unmonitored setting or in absence of resuscitative equipment. (4)
- Known or suspected gastrointestinal obstruction, including paralytic ileus. (4)
- Known hypersensitivity to oxymorphone, any other ingredients in oxymorphone hydrochloride tablets. (4)
- Moderate or severe hepatic impairment. (4)

5 WARNINGS AND PRECAUTIONS

- Opioid Induced Hyperalgesia (OIH) and Allodynia: Opioid-Induced Hyperalgesia (OIH) occurs when an opioid analgesic paradoxically causes an increase in pain, or an increase in sensitivity to pain. If OIH is suspected, carefully consider appropriately decreasing the dose of the current opioid analgesic, or opioid rotation. (5.6)
- Life-Threatening Respiratory Depression in Patients with Chronic Pulmonary Disease or in Elderly, Cachectic, or Debilitated Patients:Regularly evaluate, particularly during initiation and titration. (5.7)
- Anaphylaxis, Angioedema, and Other Hypersensitivity Reactions:If symptoms occur, stop administration immediately, discontinue permanently, and do not rechallenge with any oxymorphone formulation. (5.8)
- Adrenal Insufficiency:If diagnosed, treat with physiologic replacement of corticosteroids, and wean patient off of the opioid. (5.9)
- Severe Hypotension:Regularly evaluate during dosage initiation and titration. Avoid use of oxymorphone hydrochloride tablets in patients with circulatory shock. (5.10)
- Risks of Use in Patients with Increased Intracranial Pressure, Brain Tumors, Head Injury, or Impaired Consciousness:Regularly evaluate for sedation and respiratory depression. Avoid use of oxymorphone hydrochloride tablets in patients with impaired consciousness or coma. (5.11)

6 ADVERSE REACTIONS

Adverse reactions (≥ 2% of patients): Nausea‚ pyrexia‚ somnolence‚ vomiting‚ pruritus‚ headache‚ dizziness‚ constipation‚ and confusion.

To report SUSPECTED ADVERSE REACTIONS, contact KVK-Tech, Inc. at 1-800-862-3895 or FDA at 1-800-FDA-1088 or www.fda.gov/medwatch.

7 DRUG INTERACTIONS

- Serotonergic Drugs:Concomitant use may result in serotonin syndrome. Discontinue oxymorphone hydrochloride tablets if serotonin syndrome is suspected. (7)
- Mixed Agonist/Antagonist and Partial Agonist Opioid Analgesics:Avoid use with oxymorphone hydrochloride tablets because they may reduce analgesic effect of oxymorphone hydrochloride tablets or precipitate withdrawal symptoms. (7)
- Monoamine oxidase inhibitors (MAOIs):Can potentiate the effects of oxymorphone. Avoid concomitant use in patients receiving MAOIs or within 14 days of stopping such treatment with an MAOI. (7)

8 USE IN SPECIFIC POPULATIONS

- Pregnancy:May cause fetal harm (8.1)

FULL PRESCRIBING INFORMATION

BOXED WARNING

WARNING: SERIOUS AND LIFE-THREATENING RISKS FROM USE OF OXYMORPHONE HYDROCHLORIDE TABLETS

Addiction, Abuse, and Misuse

Because the use of oxymorphone hydrochloride tablets exposes patients and other users to the risks of opioid addiction, abuse, and misuse, which can lead to overdose and deathassess each patient’s risk prior to prescribing and reassess all patients regularly for the development of these behaviors and conditions [see Warnings and Precautions (5.1)].

Life-threatening Respiratory Depression

Serious, life-threatening, or fatal respiratory depression may occur with use of oxymorphone hydrochloride tablets, especially during initiation or following a dosage increase. To reduce the risk of respiratory depression, proper dosing and titration of oxymorphone hydrochloride tablets are essential [see Warnings and Precautions (5.2)].

Accidental Ingestion

Accidental ingestion of even one dose of oxymorphone hydrochloride tablets, especially by children, can result in a fatal overdose of oxymorphone [see Warnings and Precautions (5.2)].

Risks From Concomitant Use With Benzodiazepines Or Other CNS Depressants

Concomitant use of opioids with benzodiazepines or other central nervous system (CNS) depressants, including alcohol, may result in profound sedation, respiratory depression, coma, and death. Reserve concomitant prescribing of oxymorphone hydrochloride tablets and benzodiazepines or other CNS depressants for use in patients for whom alternative treatment options are inadequate [see Warnings and Precautions (5.3), Drug Interactions (7)].

Neonatal Opioid Withdrawal Syndrome (NOWS)

Advise pregnant women using opioids for an extended period of time of the risk of Neonatal Opioid Withdrawal Syndrome, which may be lifethreatening if not recognized and treated. Ensure that management by neonatology experts will be available at delivery [see Warnings and Precautions (5.4)].

OpioidAnalgesic Risk Evaluation and Mitigation Strategy (REMS)

Healthcare providers are strongly encouraged to complete a REMS compliant education program and to counsel patients and caregivers on serious risks, safe use, and the importance of reading the Medication Guide with each prescription [see Warnings and Precautions (5.5)].

Interaction with Alcohol

Instruct patients not to consume alcoholic beverages or use prescription or non-prescription products that contain alcohol while taking oxymorphone hydrochloride tablets. The co-ingestion of alcohol with oxymorphone hydrochloride tablets may result in increased plasma levels and a potentially fatal overdose of oxymorphone [see Warnings and Precautions (5.3)].

1 INDICATIONS AND USAGE

Oxymorphone hydrochloride tablets are indicated for the management of acute pain severe enough to require an opioid analgesic and for which alternative treatments are inadequate.

Limitations of Use

Because of the risks of addiction, abuse, misuse, overdose, and death, which can occur at any dosage or duration, and persist over the course of therapy [see Warnings and Precautions (5.1)], reserve opioid analgesics, including oxymorphone hydrochloride for use in patients for whom alternative treatment options are ineffective, not tolerated, or would be otherwise inadequate to provide sufficient management of pain.

2 DOSAGE AND ADMINISTRATION

2.1 Important Dosage and Administration Instructions

Oxymorphone hydrochloride tablets should be administered on an empty stomach, at least one hour prior to or two hours after eating [see Clinical Pharmacology(12.3)].

To avoid medication errors, prescribers and pharmacists must be aware that oxymorphone is available as both immediate-release 5 mg and 10 mg tablets and extended-release 5 mg and 10 mg tablets [see Dosage Forms and Strengths(3)].

Oxymorphone hydrochloride tablets should be prescribed only by healthcare professionals who are knowledgeable about the use of opioids and how to mitigate the associated risks.

Use the lowest effective dosage for the shortest duration of time consistent with individual patient treatment goals [see Warnings and Precautions (5)]. Because the risk of overdose increases as opioid doses increase, reserve titration to higher doses of oxymorphone hydrochloride tablets for patients in whom lower doses are insufficiently effective and in whom the expected benefits of using a higher dose opioid clearly outweigh the substantial risks.

Many acute pain conditions (e.g., the pain that occurs with a number of surgical procedures or acute musculoskeletal injuries) require no more than a few days of an opioid analgesic. Clinical guidelines on opioid prescribing for some acute pain conditions are available.

There is variability in the opioid analgesic dose and duration needed to adequately manage pain due both to the cause of pain and to individual patient factors. Initiate the dosing regimen for each patient individually, taking into account the patient’s underlying cause and severity of pain, prior analgesic treatment and response, and risk factors for addiction, abuse, and misuse [see Warnings and Precautions(5.1)].

Respiratory depression can occur at any time during opioid therapy, especially when initiating and following dosage increases with oxymorphone hydrochloride tablets. Consider this risk when selecting an initial dose and when making dose adjustments [see Warnings and Precautions(5)].

2.2 Patient Access to an Opioid Overdose Reversal Agent for the Emergency Treatment of Opioid Overdose

Inform patients and caregivers about opioid overdose reversal agents (e.g., naloxone, nalmefene). Discuss the importance of having access to an opioid overdose reversal agent, especially if the patient has risk factors for overdose (e.g., concomitant use of CNS depressants, a history of opioid use disorder, or prior opioid overdose) or if there are household members (including children) or other close contacts at risk for accidental ingestion or opioid overdose. The presence of risk factors for overdose should not prevent the management of pain in any patient [see Warnings and Precautions(5.1, 5.2, 5.3)].

Discuss the options for obtaining an opioid overdose reversal agent (e.g., prescription, over-the-counter, or as part of a community-based program) [see Warnings and Precautions(5.2)].

There are important differences among the opioid overdose reversal agents, such as route of administration, product strength, approved patient age range, and pharmacokinetics. Be familiar with these differences, as outlined in the approved labeling for those products, prior to recommending or prescribing such an agent.

2.3 Initial Dosage

Use of Oxymorphone Hydrochloride Tablets as the First Opioid Analgesic

Initiate treatment with oxymorphone hydrochloride tablets in a dosing range of 10 to 20 mg every 4 to 6 hours as needed for pain, at the lowest dose necessary to achieve adequate analgesia. Titrate the dose based upon the individual patient’s response to their initial dose of oxymorphone hydrochloride tablets.

Do not initiate treatment with doses higher than 20 mg because of the potential serious adverse reactions [see Clinical Studies (14.1)].

Conversion from Other Opioids to Oxymorphone Hydrochloride Tablets

There is inter-patient variability in the potency of opioid drugs and opioid formulations. Therefore, a conservative approach is advised when determining the total daily dosage of oxymorphone hydrochloride tablets. It is safer to underestimate a patient’s 24-hour oxymorphone hydrochloride tablets dosage than to overestimate the 24-hour oxymorphone hydrochloride tablets dosage and manage an adverse reaction due to overdose.

For conversion from other opioids to oxymorphone hydrochloride tablets, physicians and other healthcare professionals are advised to refer to published relative potency information, keeping in mind that conversion ratios are only approximate. In general, it is safest to start oxymorphone hydrochloride tablets therapy by administering half of the calculated total daily dose of oxymorphone hydrochloride tablets in 4 to 6 equally divided doses, every 4-6 hours. The initial dose of oxymorphone hydrochloride tablets can be gradually adjusted until adequate pain relief and acceptable side effects have been achieved.

Conversion from Parenteral Oxymorphone to Oxymorphone Hydrochloride Tablets

Given oxymorphone hydrochloride tablet’s absolute oral bioavailability of approximately 10%, patients receiving parenteral oxymorphone may be converted to oxymorphone hydrochloride tablets by administering 10 times the patient’s total daily parenteral oxymorphone dose as oxymorphone hydrochloride tablets, in four or six equally divided doses (e.g., [IV dose x 10] divided by 4 or 6). For example, approximately 10 mg of oxymorphone hydrochloride tablets four times daily may be required to provide pain relief equivalent to a total daily IM dose of 4 mg oxymorphone. Due to patient variability with regard to opioid analgesic response, upon conversion patients should be closely monitored to ensure adequate analgesia and to minimize side effects.

Conversion from Oxymorphone Hydrochloride Tablets to Extended-Release Oxymorphone

The relative bioavailability of oxymorphone hydrochloride tablets compared to extended-release oxymorphone is unknown, so conversion to extended-release oxymorphone may lead to increased risk of excessive sedation and respiratory depression.

2.4 Dosage Modifications in Patients with Mild Hepatic Impairment

Oxymorphone hydrochloride tablets are contraindicated in patients with moderate or severe hepatic impairment.

Use oxymorphone hydrochloride tablets with caution in patients with mild hepatic impairment, starting with the lowest dose (e.g., 5 mg) and titrating slowly while carefully monitoring for signs of respiratory and central nervous system depression [see Warnings and Precautions (5.3) and Clinical Pharmacology (12.3)] .

2.5 Dosage Modifications in Patients with Renal Impairment

Use oxymorphone hydrochloride tablets with caution in patients with creatinine clearance rates less than 50 mL/min., starting with the lowest dose (e.g., 5 mg) and titrating slowly while carefully monitoring for signs of respiratory and central nervous system depression [see Warnings and Precautions (5.2) and Clinical Pharmacology (12.3)] .

2.6 Dosage Modifications in Geriatric Patients

Exercise caution in the selection of the starting dose of oxymorphone hydrochloride tablets for an elderly patient by starting with the lowest dose (e.g., 5 mg) and titrate slowly while carefully monitoring for signs of respiratory and central nervous system depression [see Use in Specific Populations (8.5) ].

2.7 Dosage Modifications with Concomitant Use of Central Nervous System Depressants

Oxymorphone hydrochloride tablets, like all opioid analgesics, should be started at one-third to one-half of the usual dose in patients who are concurrently receiving other central nervous system (CNS) depressants including sedatives or hypnotics, general anesthetics, phenothiazines, tranquilizers, and alcohol, because respiratory depression, hypotension and profound sedation, coma or death may result [see Warnings and Precautions (5.3) and Drug Interactions (7)] . When combined therapy with any of the above medications is considered, the dose of one or both agents should be reduced.

2.8 Titration and Maintenance of Therapy

Individually titrate oxymorphone hydrochloride tablets to a dose that provides adequate analgesia and minimizes adverse reactions. Continually reevaluate patients receiving oxymorphone hydrochloride tablets to assess the maintenance of pain control, signs and symptoms of opioid withdrawal, and other adverse reactions, as well as reassessing for the development of addiction, abuse, or misuse [see Warnings and Precautions (5.1, 5.14)].Frequent communication is important among the prescriber, other members of the healthcare team, the patient, and the caregiver/family during periods of changing analgesic requirements, including initial titration.

If the level of pain increases after dosage stabilization, attempt to identify the source of increased pain before increasing the oxymorphone hydrochloride tablets dosage. If after increasing the dosage, unacceptable opioid-related adverse reactions are observed (including an increase in pain after dosage increase), consider reducing the dosage [see Warnings and Precautions (5)]. Adjust the dosage to obtain an appropriate balance between management of pain and opioid-related adverse reactions.

2.9 Safe Reduction or Discontinuation of Oxymorphone Hydrochloride Tablets

Do not rapidly reduce or abruptly discontinue oxymorphone hydrochloride tablets in patients who may be physically dependent on opioids. Rapid reduction or abrupt discontinuation of opioid analgesics in patients who are physically dependent on opioids has resulted in serious withdrawal symptoms, uncontrolled pain, and suicide. Rapid reduction or abrupt discontinuation has also been associated with attempts to find other sources of opioid analgesics, which may be confused with drug-seeking for abuse. Patients may also attempt to treat their pain or withdrawal symptoms with illicit opioids, such as heroin, and other substances.

When a decision has been made to decrease the dose or discontinue therapy in an opioid-dependent patient taking oxymorphone hydrochloride tablets, there are a variety of factors that should be considered, including the total daily dose of opioid (including Oxymorphone Hydrochloride Tablets) the patient has been taking, the duration of treatment, the type of pain being treated, and the physical and psychological attributes of the patient. It is important to ensure ongoing care of the patient and to agree on an appropriate tapering schedule and follow-up plan so that patient and provider goals and expectations are clear and realistic. When opioid analgesics are being discontinued due to a suspected substance use disorder, evaluate and treat the patient, or refer for evaluation and treatment of the substance use disorder. Treatment should include evidence-based approaches, such as medication assisted treatment of opioid use disorder. Complex patients with comorbid pain and substance use disorders may benefit from referral to a specialist.

There are no standard opioid tapering schedules that are suitable for all patients. Good clinical practice dictates a patient-specific plan to taper the dose of the opioid gradually. For patients on oxymorphone hydrochloride Tablets who are physically opioid-dependent, initiate the taper by a small enough increment (e.g., no greater than 10% to 25% of the total daily dose) to avoid withdrawal symptoms, and proceed with dose-lowering at an interval of every 2 to 4 weeks. Patients who have been taking opioids for briefer periods of time may tolerate a more rapid taper.

It may be necessary to provide the patient with lower dosage strengths to accomplish a successful taper. Reassess the patient frequently to manage pain and withdrawal symptoms, should they emerge. Common withdrawal symptoms include restlessness, lacrimation, rhinorrhea, yawning, perspiration, chills, myalgia, and mydriasis. Other signs and symptoms also may develop, including irritability, anxiety, backache, joint pain, weakness, abdominal cramps, insomnia, nausea, anorexia, vomiting, diarrhea, or increased blood pressure, respiratory rate, or heart rate. If withdrawal symptoms arise, it may be necessary to pause the taper for a period of time or raise the dose of the opioid analgesic to the previous dose, and then proceed with a slower taper. In addition, evaluate patients for any changes in mood, emergence of suicidal thoughts, or use of other substances.

When managing patients taking opioid analgesics, particularly those who have been treated for an extended period of time, and/or with high doses for chronic pain, ensure that a multimodal approach to pain management, including mental health support (if needed), is in place prior to initiating an opioid analgesic taper. A multimodal approach to pain management may optimize the treatment of chronic pain, as well as assist with the successful tapering of the opioid analgesic [see Warnings and Precautions (5.13), Drug Abuse and Dependence (9.3)].

3 DOSAGE FORMS AND STRENGTHS

Oxymorphone Hydrochloride Tablets, USP are available as 5 mg and 10 mg for oral administration.

5 mg tablet is supplied as a blue, round, biconvex tablet debossed with “K” above “70” on one side and plain on the other.

10 mg tablet is supplied as a red, round, biconvex tablet debossed with “K” above “71” on one side and plain on the other.

4 CONTRAINDICATIONS

Oxymorphone hydrochloride tablets are contraindicated in patients with:

- Significant respiratory depression [see Warnings and Precautions (5.2)]
- Acute or severe bronchial asthma in an unmonitored setting or in the absence of resuscitative equipment [see Warnings and Precautions (5.7)]
- Known or suspected gastrointestinal obstruction, including paralytic ileus [see Warnings and Precautions (5.12)]
- Hypersensitivity to oxymorphone (e.g., anaphylaxis, angioedema) or [see Warnings and precautions (5.8), Adverse Reactions (6)]
- Moderate or severe hepatic impairment [see Warnings and Precautions (5.16)

5 WARNINGS AND PRECAUTIONS

5.1 Addiction, Abuse, and Misuse

Oxymorphone hydrochloride tablets contains oxymorphone, a Schedule II controlled substance. As an opioid, oxymorphone hydrochloride tablets exposes users to the risks of addiction, abuse, and misuse [see Drug Abuse and Dependence (9)].

Although the risk of addiction in any individual is unknown, it can occur in patients appropriately prescribed oxymorphone hydrochloride tablets. Addiction can occur at recommended dosages and if the drug is misused or abused. The risk of opioid-related overdose or overdose-related death is increased with higher opioid doses, and this risk persists over the course of therapy. In postmarketing studies, addiction, abuse, misuse, and fatal and non-fatal opioid overdose were observed in patients with long-term opioid use [see Adverse Reactions (6.2)].

Assess each patient’s risk for opioid addiction, abuse, or misuse prior to prescribing oxymorphone hydrochloride tablets, and reassess all patients receiving oxymorphone hydrochloride tablets for the development of these behaviors and conditions. Risks are increased in patients with a personal or family history of substance abuse (including drug or alcohol abuse or addiction) or mental illness (e.g., major depression). The potential for these risks should not, however, prevent the proper management of pain in any given patient. Patients at increased risk may be prescribed opioids such as oxymorphone hydrochloride tablets, but use in such patients necessitates intensive counseling about the risks and proper use of oxymorphone hydrochloride tablets along with frequent reevaluation for signs of addiction, abuse, and misuse. Consider recommending or prescribing an opioid overdose reversal agent [see Dosage and Administration (2.2), Warnings and Precautions (5.3)].

Opioids are sought for non-medical use and are subject to diversion from legitimate prescribed use. Consider these risks when prescribing or dispensing oxymorphone hydrochloride tablets. Strategies to reduce these risks include prescribing the drug in the smallest appropriate quantity and advising the patient on careful storage of the drug during the course of treatment and the proper disposal of unused drug. Contact local state professional licensing board or state-controlled substances authority for information on how to prevent and detect abuse or diversion of this product.

5.2 Life-Threatening Respiratory Depression

Serious, life-threatening, or fatal respiratory depression has been reported with the use of opioids, even when used as recommended. Respiratory depression, if not immediately recognized and treated, may lead to respiratory arrest and death. Management of respiratory depression may include close observation, supportive measures, and use of opioid overdose reversal agents (e.g., naloxone, nalmefene), depending on the patient’s clinical status [see Overdosage (10)]. Carbon dioxide (CO2) retention from opioid-induced respiratory depression can exacerbate the sedating effects of opioids.

While serious, life-threatening, or fatal respiratory depression can occur at any time during the use of oxymorphone hydrochloride tablets, the risk is greatest during the initiation of therapy or following a dosage increase of oxymorphone hydrochloride tablets.

To reduce the risk of respiratory depression, proper dosing and titration of oxymorphone hydrochloride tablets are essential [see Dosage and Administration (2)]. Overestimating the oxymorphone hydrochloride tablets dosage when converting patients from another opioid product can result in a fatal overdose with the first dose.

Accidental ingestion of even one dose of oxymorphone hydrochloride tablets, especially by children, can result in respiratory depression and death due to an overdose of oxymorphone.

Educate patients and caregivers on how to recognize respiratory depression and emphasize the importance of calling 911 or getting emergency medical help right away in the event of a known or suspected overdose [see Patient Counseling Information (17)].

Opioids can cause sleep-related breathing disorders including central sleep apnea (CSA) and sleep-related hypoxemia. Opioid use increases the risk of CSA in a dose-dependent fashion. In patients who present with CSA, consider decreasing the opioid dosage using best practices for opioid taper [see Dosage and Administration (2.5)].

Patient Access to an Opioid Overdose Reversal Agent for the Emergency Treatment of Opioid Overdose

Inform patients and caregivers about opioid overdose reversal agents (e.g., naloxone, nalmefene). Discuss the importance of having access to an opioid overdose reversal agent, especially if the patient has risk factors for overdose (e.g., concomitant use of CNS depressants, a history of opioid use disorder, or prior opioid overdose) or if there are household members (including children) or other close contacts at risk for accidental ingestion or opioid overdose. The presence of risk factors for overdose should not prevent the management of pain in any patient [see Warnings and Precautions (5.1, 5.3)].

Discuss the options for obtaining an opioid overdose reversal agent (e.g., prescription, over-the-counter, or as part of a community-based program).

There are important differences among the opioid overdose reversal agents, such as route of administration, product strength, approved patient age range, and pharmacokinetics. Be familiar with these differences, as outlined in the approved labeling for those products, prior to recommending or prescribing such an agent.

Educate patients and caregivers on how to recognize respiratory depression, and how to use an opioid overdose reversal agent for the emergency treatment of opioid overdose. Emphasize the importance of calling 911 or getting emergency medical help, even if an opioid overdose reversal agent is administered [see Dosage and Administration (2.2), Warnings and Precautions (5.1, 5.3), Overdosage (10)].

5.3 Risks from Concomitant Use with Benzodiazepines or Other CNS Depressants

Patients must not consume alcoholic beverages or prescription or non-prescription products containing alcohol while on oxymorphone hydrochloride tablets therapy. The co-ingestion of alcohol with oxymorphone hydrochloride tablets may result in increased plasma levels and a potentially fatal overdose of oxymorphone [see Clinical Pharmacology (12.3)].

Profound sedation, respiratory depression, coma, and death may result from the concomitant use of oxymorphone hydrochloride tablets with benzodiazepines and/or other CNS depressants, including alcohol (e.g., non-benzodiazepine sedatives/hypnotics, anxiolytics, gabapentinoids [gabapentin or pregabalin], tranquilizers, muscle relaxants, general anesthetics, antipsychotics, other opioids). Because of these risks, reserve concomitant prescribing of these drugs for use in patients for whom alternative treatment options are inadequate.

Observational studies have demonstrated that concomitant use of opioid analgesics and benzodiazepines increases the risk of drug-related mortality compared to use of opioid analgesics alone. Because of similar pharmacological properties, it is reasonable to expect similar risk with the concomitant use of other CNS depressant drugs with opioid analgesics [see Drug Interactions (7)].

If the decision is made to prescribe a benzodiazepine or other CNS depressant concomitantly with an opioid analgesic, prescribe the lowest effective dosages and minimum durations of concomitant use. In patients already receiving an opioid analgesic, prescribe a lower initial dose of the benzodiazepine or other CNS depressant than indicated in the absence of an opioid, and titrate based on clinical response. If an opioid analgesic is initiated in a patient already taking a benzodiazepine or other CNS depressant, prescribe a lower initial dose of the opioid analgesic, and titrate based on clinical response. Inform patients and caregivers of this potential interaction, educate them on the signs and symptoms of respiratory depression (including sedation).

If concomitant use is warranted, consider recommending or prescribing an opioid overdose reversal agent [see Dosage and Administration (2.2), Warnings and Precautions (5.3), Overdosage (10)].

Advise both patients and caregivers about the risks of respiratory depression and sedation when oxymorphone hydrochloride tablets are used with benzodiazepines or other CNS depressants (including alcohol and illicit drugs). Advise patients not to drive or operate heavy machinery until the effects of concomitant use of the benzodiazepine or other CNS depressant have been determined. Screen patients for risk of substance use disorders, including opioid abuse and misuse, and warn them of the risk for overdose and death associated with the use of additional CNS depressants including alcohol and illicit drugs [see Drug Interactions (7), Patient Counseling Information (17)].

5.4 Neonatal Opioid Withdrawal Syndrome

Use of oxymorphone hydrochloride tablets for an extended period of time during pregnancy can result in withdrawal in the neonate. Neonatal opioid withdrawal syndrome, unlike opioid withdrawal syndrome in adults, may be life-threatening if not recognized and treated, and requires management according to protocols developed by neonatology experts. Observe newborns for signs of neonatal opioid withdrawal syndrome and manage accordingly. Advise pregnant women using opioids for for an extended period of time of the risk of neonatal opioid withdrawal syndrome and ensure that appropriate treatment will be available [see Use in Specific Populations (8.1), Patient Counseling Information (17)].

5.5 Risk Evaluation and Mitigation Strategy (REMS)

To ensure that the benefits of opioid analgesics outweigh the risks of addiction, abuse, and misuse, the Food and Drug Administration (FDA) has required a Risk Evaluation and Mitigation Strategy (REMS) for these products. Under the requirements of the REMS, drug companies with approved opioid analgesic products must make REMS-compliant education programs available to healthcare providers. Healthcare providers are strongly encouraged to do all of the following:

- Complete a REMS-compliant education programoffered by an accredited provider of continuing education (CE) or another education program that includes all the elements of the FDA Education Blueprint for Health Care Providers Involved in the Management or Support of Patients with Pain.

- Discuss the safe use, serious risks, and proper storage and disposal of opioid analgesics with patients and/or their caregivers every time these medicines are prescribed. The Patient Counseling Guide (PCG) can be obtained at this link: www.fda.gov/OpioidAnalgesicREMSPCG.

- Emphasize to patients and their caregivers the importance of reading the Medication Guide that they will receive from their pharmacist every time an opioid analgesic is dispensed to them.

- Consider using other tools to improve patient, household, and community safety, such as patient prescriber agreements that reinforce patient-prescriber responsibilities.

To obtain further information on the opioid analgesic REMS and for a list of accredited REMS CME/CE, call 1-800-503-0784, or log on to www.opioidanalgesicrems.com. The FDA Blueprint can be found at www.fda.gov/OpioidAnalgesicREMSBlueprint.

5.6 Opioid-Induced Hyperalgesia and Allodynia

Opioid-Induced Hyperalgesia (OIH) occurs when an opioid analgesic paradoxically causes an increase in pain, or an increase in sensitivity to pain. This condition differs from tolerance, which is the need for increasing doses of opioids to maintain a defined effect [see Dependence (9.3)]. Symptoms of OIH include (but may not be limited to) increased levels of pain upon opioid dosage increase, decreased levels of pain upon opioid dosage decrease, or pain from ordinarily non-painful stimuli (allodynia). These symptoms may suggest OIH only if there is no evidence of underlying disease progression, opioid tolerance, opioid withdrawal, or addictive behavior.

Cases of OIH have been reported, both with short-term and longer-term use of opioid analgesics. Though the mechanism of OIH is not fully understood, multiple biochemical pathways have been implicated. Medical literature suggests a strong biologic plausibility between opioid analgesics and OIH and allodynia. If a patient is suspected to be experiencing OIH, carefully consider appropriately decreasing the dose of the current opioid analgesic, or opioid rotation (safely switching the patient to a different opioid moiety) [see Dosage and Administration (2.1); Warnings and Precautions (5.6)].

5.7 Life-Threatening Respiratory Depression in Patients with Chronic Pulmonary Disease or in Elderly, Cachectic, or Debilitated Patients

The use of oxymorphone hydrochloride tablets in patients with acute or severe bronchial asthma in an unmonitored setting or in the absence of resuscitative equipment is contraindicated.

Patients with Chronic Pulmonary Disease:Oxymorphone hydrochloride tablets-treated patients with significant chronic obstructive pulmonary disease or cor pulmonale, and those with a substantially decreased respiratory reserve, hypoxia, hypercapnia, or pre-existing respiratory depression are at increased risk of decreased respiratory drive including apnea, even at recommended dosages of oxymorphone hydrochloride tablets [see Warnings and Precautions (5.2)].

Elderly, Cachectic, or Debilitated Patients:Life-threatening respiratory depression is more likely to occur in elderly, cachectic, or debilitated patients because they may have altered pharmacokinetics or altered clearance compared to younger, healthier patients [see Warnings and Precautions (8.5)].

Regularly evaluate patients, particularly when initiating and titrating oxymorphone hydrochloride tablets and when oxymorphone hydrochloride tablets are given concomitantly with other drugs that depress respiration [see Use in Specific Populations (8.5)].

Alternatively, consider the use of non-opioid analgesics in these patients.

5.8 Anaphylaxis, Angioedema, and Other Hypersensitivity Reactions

Potentially life-threatening hypersensitivity reactions, including anaphylaxis and angioedema, have occurred in patients treated with oxymorphone hydrochloride tablets in the postmarket setting. The most commonly described clinical features in these reports were swelling of the face, eyes, mouth, lips, tongue, hands, and/or throat; dyspnea; hives, pruritus, and/or rash; and nausea/vomiting. If anaphylaxis or other hypersensitivity occurs, stop administration of oxymorphone hydrochloride tablets immediately, discontinue oxymorphone hydrochloride tablets permanently, and do not rechallenge with any formulation of oxymorphone. Advise patients to seek immediate medical attention if they experience any symptoms of a hypersensitivity reaction [see Patient Counseling Information (17)].

5.9 Adrenal Insufficiency

Cases of adrenal insufficiency have been reported with opioid use, more often following greater than one month of use. Presentation of adrenal insufficiency may include non-specific symptoms and signs including nausea, vomiting, anorexia, fatigue, weakness, dizziness, and low blood pressure. If adrenal insufficiency is suspected, confirm the diagnosis with diagnostic testing as soon as possible. If adrenal insufficiency is diagnosed, treat with physiologic replacement doses of corticosteroids. Wean the patient off of the opioid to allow adrenal function to recover and continue corticosteroid treatment until adrenal function recovers. Other opioids may be tried as some cases reported use of a different opioid without recurrence of adrenal insufficiency. The information available does not identify any particular opioids as being more likely to be associated with adrenal insufficiency.

5.10 Severe Hypotension

Oxymorphone hydrochloride tablets may cause severe hypotension including orthostatic hypotension and syncope in ambulatory patients. There is increased risk in patients whose ability to maintain blood pressure has already been compromised by a reduced blood volume or concurrent administration of certain CNS depressant drugs (e.g., phenothiazines or general anesthetics) [see Warnings and Precautions (5.5) and Drug Interactions (7)]. Regularly evaluate these patients for signs of hypotension after initiating or titrating the dosage of oxymorphone hydrochloride tablets. In patients with circulatory shock, oxymorphone hydrochloride tablets may cause vasodilation that can further reduce cardiac output and blood pressure. Avoid the use of oxymorphone hydrochloride tablets in patients with circulatory shock.

5.11 Risks of Use in Patients with Increased Intracranial Pressure, Brain Tumors, Head Injury, or Impaired Consciousness

In patients who may be susceptible to the intracranial effects of CO2retention (e.g., those with evidence of increased intracranial pressure or brain tumors), oxymorphone hydrochloride tablets may reduce respiratory drive, and the resultant CO2retention can further increase intracranial pressure. Monitor such patients for signs of sedation and respiratory depression, particularly when initiating therapy with oxymorphone hydrochloride tablets.

Opioids may also obscure the clinical course in a patient with a head injury. Avoid the use of oxymorphone hydrochloride tablets in patients with impaired consciousness or coma.

5.12 Risks of Gastrointestinal Complications

Oxymorphone hydrochloride tablet is contraindicated in patients with known or suspected gastrointestinal obstruction, including paralytic ileus.

The oxymorphone in oxymorphone hydrochloride tablets may cause spasm of the sphincter of Oddi. Opioids may cause increases in serum amylase. Regularly evaluate patients with biliary tract disease, including acute pancreatitis for worsening symptoms.

Cases of opioid-induced esophageal dysfunction (OIED) have been reported in patients taking opioids. The risk of OIED may increase as the dose and/or duration of opioids increases. Regularly evaluate patients for signs and symptoms of OIED (e.g., dysphagia, regurgitation, non-cardiac chest pain) and, if necessary, adjust opioid therapy as clinically appropriate [see Clinical Pharmacology (12.2)].

5.13 Increased Risk of Seizures in Patients with Seizure Disorders

The oxymorphone in oxymorphone hydrochloride tablets may increase the frequency of seizures in patients with seizure disorders, and may increase the risk of seizures occurring in other clinical settings associated with seizures. Regularly evaluate patients with a history of seizure disorders for worsened seizure control during oxymorphone hydrochloride tablets therapy.

5.14 Withdrawal

Do not rapidly reduce or abruptly discontinue oxymorphone hydrochloride tablets in a patient physically dependent on opioids. When discontinuing oxymorphone hydrochloride tablets in a physically dependent patient, gradually taper the dosage. Rapid tapering of oxymorphone in a patient physically dependent on opioids may lead to a withdrawal syndrome and return of pain [see Dosage and Administration (2.8), Drug Abuse and Dependence (9.3)].

Additionally, avoid the use of mixed agonist/antagonist (e.g., pentazocine, nalbuphine, and butorphanol) or partial agonist (e.g., buprenorphine) analgesics in patients who are receiving a full opioid agonist analgesic, including oxymorphone hydrochloride tablets. In these patients, mixed agonist/antagonist and partial agonist analgesics may reduce the analgesic effect and/or precipitate withdrawal symptoms [see Drug Interactions (7)].

5.15 Risks of Driving and Operating Machinery

Oxymorphone hydrochloride tablets may impair the mental or physical abilities needed to perform potentially hazardous activities such as driving a car or operating machinery. Warn patients not to drive or operate dangerous machinery unless they are tolerant to the effects of oxymorphone hydrochloride tablets and know how they will react to the medication.

5.16 Hepatic Impairment

A study of extended-release oxymorphone tablets in patients with hepatic disease indicated greater plasma concentrations than in those with normal hepatic function [see Clinical Pharmacology (12.3)]. Use oxymorphone hydrochloride tablets with caution in patients with mild impairment, starting with the lowest dose and titrating slowly while carefully monitoring for side effects [see Dosage and Administration (2.3, 2.4)]. Oxymorphone hydrochloride tablets are contraindicated in patients with moderate or severe hepatic impairment.

6 ADVERSE REACTIONS

The following serious adverse reactions are described, or described in greater detail, in other sections:

- Addiction, Abuse, and Misuse [see Warnings and Precautions (5.1)]
- Life-Threatening Respiratory Depression [see Warnings and Precautions (5.2)]
- Neonatal Opioid Withdrawal Syndrome [see Warnings and Precautions (5.4)]
- Interactions with Benzodiazepines or Other CNS Depressants [see Warnings and Precautions (5.3)]
- Opioid-Induced Hyperalgesia and Allodynia [see Warnings and Precautions (5.6)]
- Anaphylaxis, Angioedema, and Other Hypersensitivity Reactions [see Warnings and Precautions (5.8)]
- Adrenal Insufficiency [see Warnings and Precautions (5.9)]
- Severe Hypotension [see Warnings and Precautions (5.10)]
- Gastrointestinal Adverse Reactions [see Warnings and Precautions (5.12)]
- Seizures [see Warnings and Precautions (5.13)]
- Withdrawal [see Warnings and Precautions (5.14)]

6.1 Clinical Trials Experience

Because clinical trials are conducted under widely varying conditions, adverse reaction rates observed in the clinical trials of a drug cannot be directly compared to rates in the clinical trials of another drug and may not reflect the rates observed in practice.

A total of 591 patients were treated with oxymorphone hydrochloride tablets in controlled clinical trials. The clinical trials consisted of patients with acute post-operative pain (n=557) and cancer pain (n=34) trials.

The following table lists adverse reactions that were reported in at least 2% of patients receiving oxymorphone hydrochloride tablets in placebo-controlled trials (acute post-operative pain (N=557)).

Table 1: Adverse Reactions Reported in Placebo-Controlled Trials
MedDRA Preferred Term | Oxymorphone Hydrochloride Tablets (N=557) | Placebo (N=270)
Nausea | 19% | 12%
Pyrexia | 14% | 8%
Somnolence | 9% | 2%
Vomiting | 9% | 7%
Pruritus | 8% | 4%
Headache | 7% | 4%
Dizziness (Excluding Vertigo) | 7% | 2%
Constipation | 4% | 1%
Confusion | 3% | <1%

The common (≥1% - <10%) adverse drug reactions reported at least once by patients treated with oxymorphone hydrochloride tablets in the clinical trials organized by MedDRA’s (Medical Dictionary for Regulatory Activities) System Organ Class were and not represented in Table 1:

Cardiac disorders:tachycardia

Gastrointestinal disorders:dry mouth, abdominal distention, and flatulence

General disorders and administration site conditions:sweating increased

Nervous system disorders:anxiety and sedation

Respiratory, thoracic and mediastinal disorders:hypoxia

Vascular disorders:hypotension

Other less common adverse reactions known with opioid treatment that were seen <1% in the oxymorphone hydrochloride tablets trials includes the following:

Abdominal pain, ileus, diarrhea, agitation, disorientation, restlessness, feeling jittery, hypersensitivity, allergic reactions, bradycardia, central nervous system depression, depressed level of consciousness, lethargy, mental impairment, mental status changes, fatigue, depression, clamminess, flushing, hot flashes, dehydration, dermatitis, dyspepsia, dysphoria, edema, euphoric mood, hallucination, hypertension, insomnia, miosis, nervousness, palpitation, postural hypotension, syncope, dyspnea, respiratory depression, respiratory distress, respiratory rate decreased, oxygen saturation decreased, difficult micturition, urinary retention, urticaria, vision blurred, visual disturbances, weakness, appetite decreased, and weight decreased.

6.2 Post-marketing Experience

The following adverse reactions have been identified during post approval use of opioids. Because these reactions are reported voluntarily from a population of uncertain size, it is not always possible to reliably estimate their frequency or establish a causal relationship to drug exposure.

Nervous system disorder: amnesia, convulsion, memory impairment.

Serotonin syndrome: Cases of serotonin syndrome, a potentially life-threatening condition, have been reported during concomitant use of opioids with serotonergic drugs.

Adrenal insufficiency: Cases of adrenal insufficiency have been reported with opioid use, more often following greater than one month of use.

Anaphylaxis: Anaphylaxis has been reported with ingredients contained in oxymorphone hydrochloride tablets.

Immune System Disorders: Angioedema, and other hypersensitivity reactions:

Androgen deficiency: Cases of androgen deficiency have occurred chronic use of opioids for an extended period of time.

Hyperalgesia and Allodynia: Cases of hyperalgesia and allodynia have been reported with opioid therapy of any duration [see Warnings and Precautions (5.6)]

Hypoglycemia: Cases of hypoglycemia have been reported in patients taking opioids. Most reports were in patients with at least one predisposing risk factor (e.g., diabetes).

Opioid-induced esophageal dysfunction (OIED): Cases of OIED have been reported in patients taking opioids and may occur more frequently in patients taking higher doses of opioids, and/or in patients taking opioids longer term [see Warnings and Precautions (5.12)].

Adverse Reactions from Observational Studies

A prospective, observational cohort study estimated the risks of addiction, abuse, and misuse in patients initiating long-term use of Schedule II opioid analgesics between 2017 and 2021. Study participants included in one or more analyses had been enrolled in selected insurance plans or health systems for at least one year, were free of at least one outcome at baseline, completed a minimum number of follow-up assessments, and either: 1) filled multiple extended-release/long-acting opioid analgesic prescriptions during a 90 day period (n=978); or 2) filled any Schedule II opioid analgesic prescriptions covering at least 70 of 90 days (n=1,244). Those included also had no dispensing of the qualifying opioids in the previous 6 months.

Over 12 months:

- approximately 1% to 6% of participants across the two cohorts newly met criteria for addiction, as assessed with two validated interview-based measures of moderate-to-severe opioid use disorder based on Diagnostic and Statistical Manual of Mental Disorders, Fifth Edition (DSM-5) criteria, and
- approximately 9% and 22% of participants across the two cohorts newly met criteria for prescription opioid abuse and misuse [defined in Drug Abuse and Dependence (9.2)], respectively, as measured with a validated self-reported instrument

A retrospective, observational cohort study estimated the risk of opioid-involved overdose or opioid overdose-related death in patients with new long-term use of Schedule II opioid analgesics from 2006 through 2016 (n=220,249). Included patients had been enrolled in either one of two commercial insurance programs, one managed care program, or one Medicaid program for at least 9 months. New long-term use was defined as having Schedule II opioid analgesic prescriptions covering at least 70 days’ supply over the 3 months prior to study entry and none during the preceding 6 months. Patients were excluded if they had an opioid-involved overdose in the 9 months prior to study entry. Overdose was measured using a validated medical code-based algorithm with linkage to the National Death Index database. The 5-year cumulative incidence estimates for opioid-involved overdose or opioid overdose-related death ranged from approximately 1.5% to 4% across study sites, counting only the first event during follow-up. Approximately 17% of first opioid overdoses observed over the entire study period (5-11 years, depending on the study site) were fatal. Higher baseline opioid dose was the strongest and most consistent predictor of opioid-involved overdose or opioid overdose-related death. Study exclusion criteria may have selected patients at lower risk of overdose, and substantial loss to follow-up (approximately 80%) also may have biased estimates.

The risk estimates from the studies described above may not be generalizable to all patients receiving opioid analgesics, such as those with exposures shorter or longer than the duration evaluated in the studies.

7 DRUG INTERACTIONS

Table 2 includes clinically significant drug interactions with oxymorphone hydrochloride tablets.

Table 2: Clinically Significant Drug Interactions with Oxymorphone Hydrochloride Tablets

Alcohol
Clinical Impact: | The concomitant use of alcohol with oxymorphone hydrochloride tablets can result in an increase of oxymorphone plasma levels and potentially fatal overdose of oxymorphone.
Intervention: | Instruct patients not to consume alcoholic beverages or use prescription or non-prescription products containing alcohol while on oxymorphone hydrochloride tablets therapy [see Clinical Pharmacology 12.3)].
Benzodiazepines and Other Central Nervous System (CNS) Depressants
Clinical Impact: | Due to additive pharmacologic effect, the concomitant use of benzodiazepines and other CNS depressants, including alcohol, can increase the risk of hypotension, respiratory depression, profound sedation, coma, and death.
Intervention: | Reserve concomitant prescribing of these drugs for use in patients for whom alternative treatment options are inadequate. Limit dosages and durations to the minimum required. Inform patients and caregivers of this potential interaction, educate them on the signs and symptoms of respiratory depression (including sedation). If concomitant use is warranted, consider recommending or prescribing an opioid overdose reversal agent [see Dosage and Administration (2.2), Warnings and Precautions (5.2, 5.3, 5.7)].
Examples: | Benzodiazepines and other sedatives/hypnotics, anxiolytics tranquilizers, muscle relaxants, general anesthetics, antipsychotics, gabapentinoids (gabapentin or pregabalin), other opioids, alcohol.
Serotonergic Drugs
Clinical Impact: | The concomitant use of opioids with other drugs that affect the serotonergic neurotransmitter system has resulted in serotonin syndrome .
Intervention: | If concomitant use is warranted, frequently evaluate the patient, particularly during treatment initiation and dose adjustment. Discontinue oxymorphone hydrochloride tablets if serotonin syndrome is suspected.
Examples: | Selective serotonin reuptake inhibitors (SSRIs), serotonin and norepinephrine reuptake inhibitors (SNRIs), tricyclic antidepressants (TCAs), triptans, 5-HT3 receptor antagonists, drugs that affect the serotonin neurotransmitter system (e.g., mirtazapine, trazodone, tramadol), certain muscle relaxants (i.e., cyclobenzaprine, metaxalone), monoamine oxidase (MAO) inhibitors (those intended to treat psychiatric disorders and also others, such as linezolid and intravenous methylene blue).
Monoamine Oxidase Inhibitors (MAOIs)
Clinical Impact: | MAOI interactions with opioids may manifest as serotonin syndrome or opioid toxicity (e.g., respiratory depression, coma) [see Warnings and Precautions (5.3)].; If urgent use of an opioid is necessary, use test doses and frequent titration of small doses to treat pain while closely monitoring blood pressure and signs and symptoms of CNS and respiratory depression.
Intervention: | The use of oxymorphone hydrochloride tablets is not recommended for patients taking MAOIs or within 14 days of stopping such treatment.
Examples: | phenelzine, tranylcypromine, linezolid
Mixed Agonist/Antagonist and Partial Agonist Opioid Analgesics
Clinical Impact: | May reduce the analgesic effect of oxymorphone hydrochloride tablets and/or may precipitate withdrawal symptoms.
Intervention: | Avoid concomitant use.
Examples: | Butorphanol, nalbuphine, pentazocine, buprenorphine
Muscle Relaxants
Clinical Impact: | Oxymorphone may enhance the neuromuscular blocking action of skeletal muscle relaxants and produce an increased degree of respiratory depression.
Intervention: | Because respiratory depression may be greater than otherwise expected, decrease the dosage of oxymorphone hydrochloride tablets and/or the muscle relaxant as necessary. Due to the risk of respiratory depression with concomitant use of skeletal muscle relaxants and opioids, consider recommending or prescribing an opioid overdose reversal agent [see Dosage and Administration (2.2), Warnings and Precautions (5.3, 5.4)]
Examples: | Cyclobenzaprine, metaxalone.
Diuretics
Clinical Impact: | Opioids can reduce the efficacy of diuretics by inducing the release of antidiuretic hormone.
Intervention: | Evaluate patients for signs of urinary retention or reduced gastric motility when oxymorphone hydrochloride tablets are used concomitantly with anticholinergic drugs.
Anticholinergic Drugs
Clinical Impact: | The concomitant use of anticholinergic drugs may increase risk of urinary retention and/or severe constipation, which may lead to paralytic ileus.
Intervention: | Evaluate patients for signs of urinary retention or reduced gastric motility when oxymorphone hydrochloride tablets are used concomitantly with anticholinergic drugs.
Cimetidine
Clinical Impact: | Cimetidine can potentiate opioid-induced respiratory depression.
Intervention: | Evaluate patients for respiratory depression when oxymorphone hydrochloride tablets and cimetidine are used concurrently.

8 USE IN SPECIFIC POPULATIONS

8.1 Pregnancy

Risk Summary

Use of opioid analgesics for an extended period of time during pregnancy may cause neonatal opioid withdrawal syndrome [see Warnings and Precautions (5.4) and Clinical Considerations]. Data from randomized controlled trials with oxymorphone use in pregnant women during labor and delivery have been conducted. However, these studies were not designed to identify a drug-associated risk for major birth defects and miscarriage because oxymorphone exposure occurred after the first trimester. There are reports of respiratory depression in infants in some of these trials [see Clinical Considerations].

In animal reproduction studies, reduced postnatal survival of pups and an increased incidence of stillborn pups were observed following oral treatment of pregnant rats with oxymorphone during gestation and through lactation at doses 2.4 and 12 times the human daily dose of 20 mg/day (HDD), respectively. Reduced fetal weights were observed with oral administration of oxymorphone to pregnant rats and rabbits during organogenesis at exposures up to 4.9 and 48.8 times the HDD, respectively [see Data]. Based on animal data, advise pregnant women of the potential risk to a fetus.

The estimated background risk of major birth defects and miscarriage for the indicated population is unknown. All pregnancies have a background risk of birth defect, loss, or other adverse outcomes. In the U.S. general population, the estimated background risk of major birth defects and miscarriage in clinically recognized pregnancies is 2-4% and 15-20%, respectively.

Clinical Considerations

Fetal/Neonatal Adverse Reactions

Use of opioid analgesics for an extended period of time during pregnancy for medical or nonmedical purposes can result in physical dependence in the neonate and neonatal opioid withdrawal syndrome shortly after birth.

Neonatal opioid withdrawal syndrome presents as irritability, hyperactivity and abnormal sleep pattern, high pitched cry, tremor, vomiting, diarrhea and failure to gain weight. The onset, duration, and severity of neonatal opioid withdrawal syndrome vary based on the specific opioid used, duration of use, timing and amount of last maternal use, and rate of elimination of the drug by the newborn. Observe newborns for symptoms of neonatal opioid withdrawal syndrome and manage accordingly [see Warnings and Precautions (5.4)].

Labor or Delivery

Opioids cross the placenta and may produce respiratory depression and psycho-physiologic effects in neonates. An opioid overdose reversal agentantagonist, such as naloxone or nalmefene, must be available for reversal of opioid-induced respiratory depression in the neonate. Oxymorphone hydrochloride tablets are not recommended for use in pregnant women during or immediately prior to labor, when other analgesic techniques are more appropriate. Opioid analgesics, including oxymorphone hydrochloride tablets, can prolong labor through actions which temporarily reduce the strength, duration, and frequency of uterine contractions. However, this effect is not consistent and may be offset by an increased rate of cervical dilation, which tends to shorten labor. Monitor neonates exposed to opioid analgesics during labor for signs of excess sedation and respiratory depression.

Data

Animal Data

Pregnant rats were treated with oxymorphone hydrochloride from Gestation Day 6 to 17 via oral gavage doses of 5, 10, or 25 mg/kg/day (2.4, 4.9, or 12.2 times the HDD based on body surface area, respectively). Reduced mean fetal weights were observed at 4.9 times the HDD. Maternal toxicity was noted in all treatment groups (reduced food consumption and body weights in all groups and mortality in the high dose group).

Pregnant rabbits were treated with oxymorphone hydrochloride from Gestation Day 7 to 20 via oral gavage doses of 10, 25, or 50 mg/kg/day (9.8, 24.4, or 48.8 times the HDD based on body surface area, respectively). Decreased mean fetal weights were noted at 48.8 times the HDD. Maternal toxicity was noted in all treatment groups (reduced food consumption and body weights).

Pregnant rats were treated with oxymorphone hydrochloride from Gestation Day 6 to Lactation Day 20 via oral gavage doses of 1, 5, 10, or 25 mg/kg/day (0.5, 2.4, 4.9, or 12.2 times the HDD based on body surface area, respectively). Increased neonatal death (postnatal day 0-1) was noted at 2.4 times the HDD. Decreased pup survival over the first week of life, reduced pup birth weight, and reduced postnatal weight gain were noted at 4.9 times the HDD. Maternal toxicity was noted in all treatment groups (reduced food consumption and body weights in all groups and mortality in the 10 and 25 mg/kg/day groups).

In a published study, neural tube defects (exencephaly and cranioschisis) were noted following subcutaneous administration of 153 mg/kg oxymorphone hydrochloride (62.2 times the HDD) on Gestation Day 8 to pregnant hamsters. This dose also produced significant maternal toxicity (20% maternal deaths).

8.2 Lactation

Risk Summary

There is no information regarding the presence of oxymorphone in human milk, the effects on the breastfed infant, or the effects on milk production. The developmental and health benefits of breastfeeding should be considered along with the mother’s clinical need for oxymorphone hydrochloride tablets and any potential adverse effects on the breastfed child from oxymorphone hydrochloride tablets or from the underlying maternal condition.

Clinical Considerations

Monitor infants exposed to oxymorphone hydrochloride tablets through breast milk for excess sedation and respiratory depression. Withdrawal symptoms can occur in breast-fed infants when maternal administration of an opioid analgesic is stopped, or when breast-feeding is stopped.

The developmental and health benefits of breastfeeding should be considered along with the mother’s clinical need for oxymorphone hydrochloride tablets and any potential adverse effects on the breastfed infant from oxymorphone hydrochloride tablets or from the underlying maternal condition.

8.3 Females and Males of Reproductive Potential

Infertility

Use of opioids for an extended period of time may cause reduced fertility in females and males of reproductive potential. It is not known whether these effects on fertility are reversible [see Clinical Pharmacology (12.2), Nonclinical Toxicology (13.1)].

8.4 Pediatric Use

Safety and effectiveness for pediatric patients, 0 to 17 years, have not been established.

An open-label study was conducted in 58 pediatric patients 12 years of age and older with postoperative pain using Oxymorphone Hydrochloride Tablets. Efficacy was not demonstrated in this population treated with doses expected to be comparable to effective starting doses in adults. In addition, pharmacokinetic results demonstrated that treatment with Oxymorphone Hydrochloride Tablets resulted in substantially higher systemic exposures to oxymorphone in 2 out of 24 patients.

Oxymorphone Hydrochloride Tablets are not recommended for use in the pediatric population

8.5 Geriatric Use

Oxymorphone hydrochloride tablets should be used with caution in elderly patients [see Clinical Pharmacology (12.3)].

Of the total number of subjects in clinical studies of oxymorphone hydrochloride tablets, 31% were 65 and over, while 7% were 75 and over. No overall differences in effectiveness were observed between these subjects and younger subjects. There were several adverse events that were more frequently observed in subjects 65 and over compared to younger subjects. These adverse events included dizziness, somnolence, confusion, and nausea. In general, dose selection for elderly patients should be cautious, usually starting at the low end of the dosing range, reflecting the greater frequency of decreased hepatic, renal or cardiac function, and of concomitant disease or other drug therapy.

Respiratory depression is the chief risk for elderly patients treated with opioids, and has occurred after large initial doses were administered to patients who were not opioid-tolerant or when opioids were co-administered with other agents that depress respiration. Titrate the dosage of oxymorphone hydrochloride tablets slowly in geriatric patients and frequently reevaluate the patient for signs of central nervous system and respiratory depression [see Warnings and Precautions (5.7)].

Oxymorphone is known to be substantially excreted by the kidney and the risk of adverse reactions to this drug may be greater in patients with impaired renal function. Because the elderly patients are more likely to have decreased renal function, care should be taken in dose selection, and it may be useful to regulatory evaluate renal function.

8.6 Hepatic Impairment

In a study of extended-release oxymorphone tablets, patients with mild hepatic impairment were shown to have an increase in bioavailability compared to the subjects with normal hepatic function. Oxymorphone hydrochloride tablets should be used with caution in patients with mild impairment. These patients should be started with the lowest dose (5 mg) and titrated slowly while carefully monitoring for signs of respiratory and central nervous system depression. Oxymorphone hydrochloride tablets are contraindicated for patients with moderate and severe hepatic impairment [see Dosage and Administration (2.4), Contraindications (4), Warnings and Precautions (5.16), and Clinical Pharmacology 12.3].

8.7 Renal Impairment

In a study of extended-release oxymorphone tablets, patients with moderate to severe renal impairment were shown to have an increase in bioavailability compared to the subjects with normal renal function [see Clinical Pharmacology (12.3)]. Such patients should be started be started with the lowest dose (5 mg) and titrated slowly while monitoring for signs of respiratory and central nervous system depression [see Dosage and Administration (2.5) Clinical Pharmacology (12.3)].

9 DRUG ABUSE AND DEPENDENCE

9.1 Controlled Substance

Oxymorphone hydrochloride tablets contains oxymorphone, a Schedule II controlled substance

9.2 Abuse

Oxymorphone hydrochloride tablets contains oxymorphone, a substance with a high potential for misuse and abuse, which can lead to the development of substance use disorder, including addiction [see Warnings and Precautions (5.1)]. Misuse is the intentional use, for therapeutic purposes, of a drug by an individual in a way other than prescribed by a healthcare provider or for whom it was not prescribed.

Abuse is the intentional, non-therapeutic use of a drug, even once, for its desirable psychological or physiological effects.

Drug addiction is a cluster of behavioral, cognitive, and physiological phenomena that may include a strong desire to take the drug, difficulties in controlling drug use (e.g., continuing drug use despite harmful consequences, giving a higher priority to drug use than other activities and obligations), and possible tolerance or physical dependence.

Misuse and abuse of oxymorphone hydrochloride tablets increases risk of overdosage, which may lead to central nervous system and respiratory depression, hypotension, seizures, and death. The risk is increased with concurrent abuse of oxymorphone hydrochloride tablets with alcohol and other CNS depressants. Abuse of and addiction to opioids in some individuals may not be accompanied by concurrent tolerance and symptoms of physical dependence. In addition, abuse of opioids can occur in the absence of addiction.

All patients treated with opioids require careful and frequent reevaluation for signs of misuse, abuse, and addiction, because use of opioid analgesic products carries the risk of addiction even under appropriate medical use. Patients at high risk of oxymorphone hydrochloride tablets abuse include those with a history of prolonged use of any opioid, including products containing oxymorphone hydrochloride, those with a history of drug or alcohol abuse, or those who use oxymorphone hydrochloride tablets in combination with other abused drugs.

“Drug-seeking” behavior is very common in persons with substance use disorders. Drug-seeking tactics include emergency calls or visits near the end of office hours, refusal to undergo appropriate examination, testing, or referral, repeated “loss” of prescriptions, tampering with prescriptions, and reluctance to provide prior medical records or contact information for other treating healthcare provider(s). “Doctor shopping” (visiting multiple prescribers to obtain additional prescriptions) is common among people who abuse drugs and people with substance use disorder. . Preoccupation with achieving adequate pain relief can be appropriate behavior in a patient with inadequate pain control.

Oxymorphone hydrochloride tablets, like other opioids, can be diverted for nonmedical use into illicit channels of distribution. Careful record-keeping of prescribing information, including quantity, frequency, and renewal requests, as required by state and federal law, is strongly advised.

Proper assessment of the patient, proper prescribing practices, periodic reevaluation of therapy, and proper dispensing and storage are appropriate measures that help to limit abuse of opioid drugs.

Risks Specific to Abuse of Oxymorphone Hydrochloride Tablets

Abuse of oxymorphone hydrochloride tablets poses a risk of overdose and death. This risk is increased with concurrent abuse of oxymorphone hydrochloride tablets with alcohol and other CNS depressants.

Parenteral drug abuse is commonly associated with transmission of infectious diseases such as hepatitis and HIV.

9.3 Dependence

Both tolerance and physical dependence can develop during use of opioid therapy.

Tolerance is a physiological state characterized by a reduced response to a drug after repeated administration (i.e., a higher dose of a drug is required to produce the same effect that was once obtained at a lower dose).

Physical dependence is a state that develops as a result of a physiological adaptation in response to repeated drug use, manifested by withdrawal signs and symptoms after abrupt discontinuation or a significant dose reduction of a drug.

Withdrawal may be precipitated through the administration of drugs with opioid antagonist activity (e.g., naloxone, nalmefene), mixed agonist/antagonist analgesics (e.g., pentazocine, butorphanol, nalbuphine), or partial agonists (e.g., buprenorphine). Physical dependence may not occur to a clinically significant degree until after several days to weeks of continued use.

Do not rapidly reduce or abruptly discontinue oxymorphone hydrochloride tablets in a patient physically dependent on opioids. Rapid tapering of oxymorphone hydrochloride tablets in a patient physically dependent on opioids may lead to serious withdrawal symptoms, uncontrolled pain, and suicide. Rapid discontinuation has also been associated with attempts to find other sources of opioid analgesics, which may be confused with drug-seeking for abuse.

When discontinuing oxymorphone hydrochloride tablets, gradually taper the dosage using a patient-specific plan that considers the following: the dose of oxymorphone hydrochloride tablets the patient has been taking, the duration of treatment, and the physical and psychological attributes of the patient. To improve the likelihood of a successful taper and minimize withdrawal symptoms, it is important that the opioid tapering schedule is agreed upon by the patient. In patients taking opioids for an extended period of time at high doses, ensure that a multimodal approach to pain management, including mental health support (if needed), is in place prior to initiating an opioid analgesic taper [see Dosage and Administration (2.8), Warnings and Precautions (5.14)].

Infants born to mothers physically dependent on opioids will also be physically dependent and may exhibit respiratory difficulties and withdrawal signs [see Use in Specific Populations (8.1)].

10 OVERDOSAGE

Clinical Presentation

Acute overdose with oxymorphone hydrochloride tablets can be manifested by respiratory depression, somnolence progressing to stupor or coma, skeletal muscle flaccidity, cold and clammy skin, constricted pupils, and, in some cases, pulmonary edema, bradycardia, hypotension, hypoglycemia, partial or complete airway obstruction, atypical snoring, and death. Marked mydriasis rather than miosis may be seen with hypoxia in overdose situations [see Clinical Pharmacology (12.2)]. Toxic leukoencephalopathy has been reported after opioid overdose and can present hours, days, or weeks after apparent recovery from the initial intoxication.

Treatment of Overdose

In case of overdose, priorities are the reestablishment of a patent and protected airway and institution of assisted or controlled ventilation, if needed. Employ other supportive measures (including oxygen and vasopressors) in the management of circulatory shock and pulmonary edema as indicated. Cardiac arrest or arrhythmias will require advanced life-support measures.

For clinically significant respiratory or circulatory depression secondary to oxymorphone overdose, administer an opioid overdose reversal agent such as naloxone or nalmefene.

Because the duration of opioid reversal is expected to be less than the duration of action of oxymorphone in oxymorphone hydrochloride tablets, carefully monitor the patient until spontaneous respiration is reliably reestablished. If the response to an opioid overdose reversal agent is suboptimal or only brief in nature, administer additional reversal agent as directed by the product’s prescribing information.

In an individual physically dependent on opioids, administration of the recommended usual dosage of the opioid overdose reversal agent will precipitate an acute withdrawal syndrome. The severity of the withdrawal symptoms experienced will depend on the degree of physical dependence and the dose of the reversal agent administered. If a decision is made to treat serious respiratory depression in the physically-dependent patient, administration of the reversal agent should begin with care and by titration with smaller than usual doses of the reversal agent.

11 DESCRIPTION

Oxymorphone Hydrochloride Tablets, USP are an opioid agonist available in 5 mg and 10 mg tablet strengths for oral administration. The chemical name for Oxymorphone hydrochloride, USP is 4, 5α-epoxy-3, 14-dihydroxy-17-methylmorphinan-6-one hydrochloride. The molecular weight is 337.80. The molecular formula is C17H19NO4•HCl and it has the following chemical structure.

Oxymorphone Hydrochloride, USP is white or slightly off-white odorless powder, which is sparingly soluble in alcohol and ether, but freely soluble in water.

The inactive ingredients in Oxymorphone Hydrochloride Tablets, USP include: lactose monohydrate, magnesium stearate, and pregelatinized maize starch. In addition, the 5 mg tablets contain FD&C blue No. 2 aluminum lake. The 10 mg tablets contain D&C red No. 30 aluminum lake.

12 CLINICAL PHARMACOLOGY

12.1 Mechanism of Action

Oxymorphone is a full opioid agonist and is relatively selective for the mu-opioid receptor, although it can bind to other opioid receptors at higher doses. The principal therapeutic action of oxymorphone is analgesia. Like all full opioid agonists, there is no ceiling effect for analgesia with oxymorphone. Clinically, dosage is titrated to provide adequate analgesia and may be limited by adverse reactions, including respiratory and CNS depression.

The precise mechanism of the analgesic action is unknown. However, specific CNS opioid receptors for endogenous compounds with opioid-like activity have been identified throughout the brain and spinal cord and are thought to play a role in the analgesic effects of this drug.

12.2 Pharmacodynamics

Effects on the Central Nervous System

Oxymorphone produces respiratory depression by direct action on brain stem respiratory centers. The respiratory depression involves a reduction in the responsiveness of the brain stem respiratory centers to both increases in carbon dioxide tension and electrical stimulation.

Oxymorphone causes miosis, even in total darkness. Pinpoint pupils are a sign of opioid overdose but are not pathognomonic (e.g., pontine lesions of hemorrhagic or ischemic origins may produce similar findings). Marked mydriasis rather than miosis may be seen due to hypoxia in overdose situations.

Effects on the Gastrointestinal Tract and Other Smooth Muscle

Oxymorphone causes a reduction in motility associated with an increase in smooth muscle tone in the antrum of the stomach and duodenum. Digestion of food in the small intestine is delayed and propulsive contractions are decreased. Propulsive peristaltic waves in the colon are decreased, while tone may be increased to the point of spasm, resulting in constipation. Other opioid-induced effects may include a reduction in biliary and pancreatic secretions, spasm of sphincter of Oddi, and transient elevations in serum amylase, and opioid-induced esophageal dysfunction (OIED).

Effects on the Cardiovascular System

Oxymorphone produces peripheral vasodilation which may result in orthostatic hypotension or syncope. Manifestations of histamine release and/or peripheral vasodilation may include pruritus, flushing, red eyes, sweating and/or orthostatic hypotension.

Effects on the Endocrine System

Opioids inhibit the secretion of adrenocorticotropic hormone (ACTH), cortisol, and luteinizing hormone (LH) in humans [see Adverse Reactions (6.2)]. They also stimulate prolactin, growth hormone (GH) secretion, and pancreatic secretion of insulin and glucagon.

Use of opioids for an extended period of time may influence the hypothalamic-pituitary-gonadal axis, leading to androgen deficiency that may manifest as low libido, impotence, erectile dysfunction, amenorrhea, or infertility. The causal role of opioids in the clinical syndrome of hypogonadism is unknown because the various medical, physical, lifestyle, and psychological stressors that may influence gonadal hormone levels have not been adequately controlled for in studies conducted to date [see Adverse Reactions (6.2)].

Effects on the Immune System

Opioids have been shown to have a variety of effects on components of the immune system in in vitro and animal models. The clinical significance of these findings is unknown. Overall, the effects of opioids appear to be modestly immunosuppressive.

Concentration–Efficacy Relationships

The minimum effective analgesic concentration varies widely among patients, especially among patients who have been previously treated with extended-release opioid agonists. The minimum effective analgesic concentration of oxymorphone for any individual patient may increase over time due to an increase in pain, the development of a new pain syndrome and/or the development of analgesic tolerance [see Dosage and Administration (2.1, 2.3)].

Concentration–Adverse Reaction Relationships

There is a relationship between increasing oxymorphone plasma concentration and increasing frequency of dose-related opioid adverse reactions such as nausea, vomiting, CNS effects, and respiratory depression. In opioid-tolerant patients, the situation may be altered by the development of tolerance to opioid-related adverse reactions [see Dosage and Administration (2.1 ,2.3 ,2.7)].

12.3 Pharmacokinetics

Absorption

The absolute oral bioavailability of oxymorphone is approximately 10%. Studies in healthy volunteers reveal predictable relationships between oxymorphone hydrochloride tablets dosage and plasma oxymorphone concentrations.

Steady-state levels were achieved after three days of multiple dose administration. Under both single-dose and steady-state conditions, dose proportionality has been established for 5 mg, 10 mg and 20 mg doses of oxymorphone hydrochloride tablets, for both peak plasma levels (Cmax) and extent of absorption (AUC) (see Table 3).

Table 3: Mean (±SD) Oxymorphone Hydrochloride Tablets Pharmacokinetic Parameters
Regimen | Dosage | Cmax; (ng/mL) | ACU; (ng·hr/mL) | T1/2; (hr)
Single Dose | 5 mg; 10 mg; 20 mg | 1.10±0.55; 1.93±0.75; 4.39±1.72 | 4.48±2.07; 9.10±3.40; 20.07±5.80 | 7.25±4.40; 7.78±3.58; 9.43±3.36
Multiple Dosea | 5 mg; 10 mg; 20 mg | 1.73±0.62; 3.51±0.91; 7.33±2.93 | 4.63±1.49; 10.19±3.34; 21.10±7.59 | NA; NA; NA
NA = not applicable
aResults after 5 days of every 6 hours dosing.

After oral dosing with 40 mg of oxymorphone hydrochloride tablets in healthy volunteers under fasting conditions or with a high-fat meal, the Cmaxand AUC were increased by approximately 38% in fed subjects relative to fasted subjects. As a result, oxymorphone hydrochloride tablets should be dosed at least one hour prior to or two hours after eating [see Dosage and Administration (2.3)].

Distribution

Formal studies on the distribution of oxymorphone in various tissues have not been conducted.

Oxymorphone is not extensively bound to human plasma proteins; binding is in the range of 10% to 12%.

Elimination

Oxymorphone Hydrochloride Tablets half-life ranges from approximately 9-11 hours after a single oral dose (5-40 mg).

Metabolism

Oxymorphone is highly metabolized, principally in the liver, and undergoes reduction or conjugation with glucuronic acid to form both active and inactive products. The two major metabolites of oxymorphone are oxymorphone-3-glucuronide and 6-OH-oxymorphone. The mean plasma AUC for oxymorphone-3-glucuronide is approximately 90-fold higher than the parent compound. The pharmacologic activity of the glucuronide metabolite has not been evaluated. 6-OH-oxymorphone has been shown in animal studies to have analgesic bioactivity. The mean plasma 6-OH-oxymorphone AUC is approximately 70% of the oxymorphone AUC following single oral doses but is essentially equivalent to the parent compound at steady-state.

Excretion

Because oxymorphone is extensively metabolized, <1% of the administered dose is excreted unchanged in the urine. On average, 33% to 38% of the administered dose is excreted in the urine as oxymorphone-3-glucuronide and 0.25% to 0.62% is excreted as 6-OH-oxymorphone in subjects with normal hepatic and renal function. In animals given radiolabeled oxymorphone, approximately 90% of the administered radioactivity was recovered within 5 days of dosing. The majority of oxymorphone-derived radioactivity was found in the urine and feces.

Specific Populations

Age: Geriatric Population

The plasma levels of oxymorphone administered as an extended-release tablet were about 40% higher in elderly (≥65 years of age) than in younger subjects [see Use in Specific Populations (8.5)].

Sex:

The effect of sex on the pharmacokinetics of oxymorphone hydrochloride tablets has not been studied. In a study with an extended-release formulation of oxymorphone, there was a consistent tendency for female subjects to have slightly higher AUCssand Cmaxvalues than male subjects. However, sex differences were not observed when AUCssand Cmaxwere adjusted by body weight.

Hepatic Impairment

The liver plays an important role in the pre-systemic clearance of orally administered oxymorphone. Accordingly, the bioavailability of orally administered oxymorphone may be markedly increased in patients with moderate to severe liver disease. The effect of hepatic impairment on the pharmacokinetics of oxymorphone hydrochloride tablets has not been studied. However, in a study with an extended-release formulation of oxymorphone, the disposition of oxymorphone was compared in 6 patients with mild, 5 patients with moderate, and one patient with severe hepatic impairment, and 12 subjects with normal hepatic function. The bioavailability of oxymorphone was increased by 1.6-fold in patients with mild hepatic impairment and by 3.7-fold in patients with moderate hepatic impairment. In one patient with severe hepatic impairment, the bioavailability was increased by 12.2-fold. The half-life of oxymorphone was not significantly affected by hepatic impairment.

Renal Impairment

The effect of renal impairment on the pharmacokinetics of oxymorphone hydrochloride tablets has not been studied. However, in a study with an extended-release formulation of oxymorphone, an increase of 26%, 57%, and 65% in oxymorphone bioavailability was observed in mild (creatinine clearance 51-80 mL/min; n=8), moderate (creatinine clearance 30-50 mL/min; n=8), and severe (creatinine clearance <30 mL/min; n=8) patients, respectively, compared to healthy controls.

Drug Interactions Studies

In vitrostudies revealed little to no biotransformation of oxymorphone to 6-OH-oxymorphone by any of the major cytochrome P450 (CYP P450) isoforms at therapeutically relevant oxymorphone plasma concentrations.

No inhibition of any of the major CYP P450 isoforms was observed when oxymorphone was incubated with human liver microsomes at concentrations of ≤50 µM. An inhibition of CYP 3A4 activity occurred at oxymorphone concentrations ≥150 µM. Therefore, it is not expected that oxymorphone, or its metabolites will act as inhibitors of any of the major CYP P450 enzymes in vivo.

Increases in the activity of the CYP 2C9 and CYP 3A4 isoforms occurred when oxymorphone was incubated with human hepatocytes. However, clinical drug interaction studies with Oxymorphone Hydrochloride Tablets ER showed no induction of CYP450 3A4 or 2C9 enzyme activity, indicating that no dose adjustment for CYP 3A4- or 2C9-mediated drug-drug interactions is required.

Alcohol Interaction

The effect of co-ingestion of alcohol with Oxymorphone Hydrochloride Tablets has not been evaluated. However, an in vivo study was performed to evaluate the effect of alcohol (40%, 20%, 4% and 0%) on the bioavailability of a single dose of 40 mg of extended-release oxymorphone tablets in healthy, fasted volunteers. Following concomitant administration of 240 mL of 40% ethanol the Cmaxincreased on average by 70% and up to 270% in individual subjects. Following the concomitant administration of 240 mL of 20% ethanol, the Cmaxincreased on average by 31% and up to 260% in individual subjects. In some individuals there was also a decrease in oxymorphone peak plasma concentrations. No effect on the release of oxymorphone from the extended-release tablet was noted in an in vitro alcohol interaction study. The mechanism of the in vivo interaction is unknown. Therefore, avoid co-administration of oxymorphone and ethanol.

13 NONCLINICAL TOXICOLOGY

13.1 Carcinogenesis, Mutagenesis, Impairment of Fertility

Carcinogenesis

No evidence of carcinogenic potential was observed in long-term animal studies in mice and rats.

Oxymorphone hydrochloride was administered to Sprague Dawley rats (2.5, 5, and 10 mg/kg/day in males and 5, 10, and 25 mg/kg/day in females) for 2 years by oral gavage. Systemic drug exposure (AUC) at the highest doses tested in male and female rats was 4.8 times and 21.2 times the human exposure at a dose of 20 mg/day, respectively. Oxymorphone hydrochloride was administered to male and female CD-1 mice (10, 25, 75 and 150 mg/kg/day) for 2 years by oral gavage. Systemic drug exposure (AUC) at 150 mg/kg/day in male and female mice was 205 times and 243 times the human exposure at a dose of 20 mg/day, respectively.

Mutagenesis

Oxymorphone hydrochloride was not mutagenic when tested in an in vitrobacterial reverse mutation assay (Ames test), or in an in vitromammalian cell chromosome aberration assay performed with human peripheral blood lymphocytes. Oxymorphone hydrochloride tested positive in both the rat and mouse in vivomicronucleus assays. An increase in micronucleated polychromatic erythrocytes occurred in mice given doses of ≥250 mg/kg and in rats given doses of 20 and 40 mg/kg. A subsequent study demonstrated that oxymorphone hydrochloride was not aneugenic in mice following administration of up to 500 mg/kg.

Additional studies indicate that the increased incidence of micronucleated polychromatic erythrocytes in rats may be secondary to increased body temperature following oxymorphone administration. Doses associated with increased micronucleated polychromatic erythrocytes also produce a marked, rapid increase in body temperature. Pretreatment of animals with sodium salicylate minimized the increase in body temperature and prevented the increase in micronucleated polychromatic erythrocytes after administration of 40 mg/kg oxymorphone.

Impairment of fertility

Female rats were treated with oxymorphone hydrochloride beginning 14 days prior to mating through Gestation Day 7 via oral gavage doses of 5, 10, or 25 mg/kg/day (2.4, 4.9, or 12.2 times the human daily dose of 20 mg/day based on body surface area, respectively). Male rats were treated via oral gavage with the same oxymorphone hydrochloride doses beginning 28 days prior to and throughout mating. In female rats, an increase in the length of the estrus cycle and decrease in the mean number of viable embryos, implantation sites and corpora lutea were observed at 4.9 times the human dose of 20 mg/day. No adverse effects of oxymorphone on male reproductive function or sperm parameters were observed.

14 CLINICAL STUDIES

The analgesic efficacy of oxymorphone hydrochloride tablets has been evaluated in acute pain following orthopedic and abdominal surgeries.

14.1 Orthopedic Surgery

Two double-blind, placebo-controlled, dose-ranging studies in patients with acute moderate to severe pain following orthopedic surgery evaluated the doses of oxymorphone hydrochloride tablets 10 mg and 20 mg, and 30 mg was included in one study. Both studies demonstrated that oxymorphone hydrochloride tablets 20 mg provided greater analgesia as measured by total pain relief based on a weighted analysis over 8 hours using a 0-4 categorical, compared to placebo. Oxymorphone hydrochloride tablets 10 mg provided greater analgesia as compared to placebo in one of the two studies. There was no evidence of superiority of the 30 mg dose over the 20 mg dose. However, there was a high rate of naloxone use in patients receiving the oxymorphone hydrochloride tablets 30 mg dose in the post-operative period [see Dosage and Administration (2.3)].

14.2 Abdominal Surgery

In a randomized, double-blind, placebo-controlled, multiple-dose study, the efficacy of oxymorphone hydrochloride tablets 10 mg and 20 mg was assessed in patients with moderate to severe acute pain following abdominal surgery. In this study, patients were dosed every 4 to 6 hours over a 48-hour treatment period. Oxymorphone hydrochloride tablets 10 and 20 mg provided greater analgesia, as measured by the mean average pain intensity on a 0-100 mm visual analog scale, over 48 hours, compared to placebo [see Dosage and Administration (2.3)].

16 HOW SUPPLIED/STORAGE AND HANDLING

Oxymorphone Hydrochloride Tablets, USP are supplied as follows:

5 mg Tablet:

Blue, round, biconvex tablets debossed with “K” above “70” on one side and plain on the other.

Bottles of 60 tablets with child-resistant closure NDC 10702-070-06

Bottles of 100 tablets with child-resistant closure NDC 10702-070-01

10 mg Tablet:

Red, round, biconvex tablets debossed with “K” above “71” on one side and plain on the other.

Bottles of 60 tablets with child-resistant closure NDC 10702-071-06

Bottles of 100 tablets with child-resistant closure NDC 10702-071-01

Store at 20° to 25°C (68° to 77°F), with excursions permitted between 15° to 30°C (59° to 86°F) [See USP Controlled Room Temperature].

Dispense in tight container as defined in the USP, with a child-resistant closure (as required).

Store Oxymorphone Hydrochloride Tablets, USP securely and dispose of properly [see Patient Counseling Information (17)].

17 PATIENT COUNSELING INFORMATION

Advise the patient to read the FDA-approved patient labeling (Medication Guide).

Storage and Disposal

Because of the risks associated with accidental ingestion, misuse, and abuse, advise patients to store oxymorphone hydrochloride tablets securely, out of sight and reach of children, and in a location not accessible by others, including visitors to the home. Inform patients that leaving oxymorphone hydrochloride tablets unsecured can pose a deadly risk to others in the home [see Warnings and Precautions(5.1, 5.2), Drug Abuse and Dependence(9.2)].

Advise patients and caregivers that when medicines are no longer needed, they should be disposed of promptly. Expired, unwanted, or unused oxymorphone hydrochloride tablets should be disposed of by flushing the unused medication down the toilet if a drug take-back option is not readily available. Inform patients that they can visit www.fda.gov/drugdisposal for a complete list of medicines recommended for disposal by flushing, as well as additional information on disposal of unused medicines.

Addiction, Abuse, and Misuse

Inform patients that the use of oxymorphone hydrochloride tablets, even when taken as recommended, can result in addiction, abuse, and misuse, which can lead to overdose and death [see Warnings and Precautions (5.1)]. Instruct patients not to share oxymorphone hydrochloride tablets with others and to take steps to protect oxymorphone hydrochloride tablets from theft or misuse.

Life-Threatening Respiratory Depression

Inform patients of the risk of life-threatening respiratory depression, including information that the risk is greatest when starting oxymorphone hydrochloride tablets or when the dosage is increased, and that it can occur even at recommended dosages.

Educate patients and caregivers on how to recognize respiratory depression and emphasize the importance of calling 911 or getting emergency medical help right away in the event of a known or suspected overdose [see Warnings and Precautions (5.2)].

Accidental Ingestion

Inform patients that accidental ingestion, especially by children, may result in respiratory depression or death [see Warnings and Precautions (5.2)].

Interactions with Benzodiazepines and Other CNS Depressants

Inform patients and caregivers that potentially fatal additive effects may occur if oxymorphone hydrochloride tablets are used with benzodiazepines or other CNS depressants, including alcohol, (e.g., non-benzodiazepines, sedative/hypnotics, anxiolytics, tranquilizers, muscle relaxants, general anesthetics, antipsychotics, gabapentinoids [gabapentin or pregabalin], and other opioids), and not to use these concomitantly unless supervised by a healthcare provider [see Warnings and Precautions (5.3), Drug Interactions (7)].

Patient Access to an Opioid Overdose Reversal Agent for the Emergency Treatment of Opioid Overdose

Inform patients and caregivers about opioid overdose reversal agents (e.g., naloxone, nalmefene). Discuss the importance of having access to an opioid overdose reversal agent, especially if the patient has risk factors for overdose (e.g., concomitant use of CNS depressants, a history of opioid use disorder, or prior opioid overdose) or if there are household members (including children) or other close contacts at risk for accidental ingestion or opioid overdose.
Discuss with the patient the options for obtaining an opioid overdose reversal agent (e.g., prescription, over-the-counter, or as part of a community-based program) [see Dosage and Administration (2.2), Warnings and Precautions (5.3)].

Educate patients and caregivers on how to recognize the signs and symptoms of an overdose.

Explain to patients and caregivers that effects of opioid overdose reversal agents like naloxone and nalmefene are temporary, and that they must call 911 or get emergency medical help right away in all cases of known or suspected opioid overdose, even if an opioid overdose reversal agent is administered [see Overdosage (10)].

Advise patients and caregivers:

- how to treat with the overdose reversal agent in the event of an opioid overdose
- to tell family and friends about their opioid overdose reversal agent, and to keep it in a place where family and friends can access it in an emergency
- to read the Patient Information (or other educational material) that will come with their opioid overdose reversal agent. Emphasize the importance of doing this before an opioid emergency happens, so the patient and caregiver will know what to do.

Hyperalgesia and Allodynia

Inform patients and caregivers not to increase opioid dosage without first consulting a clinician. Advise patients to seek medical attention if they experience symptoms of hyperalgesia, including worsening pain, increased sensitivity to pain, or new pain [see Warnings and Precautions (5.6); Adverse Reactions (6.2)].

Anaphylaxis, Angioedema, and Other Hypersensitivity Reactions

Inform patients that anaphylaxis, angioedema, and other hypersensitivity reactions have been reported with ingredients contained in oxymorphone hydrochloride tablets. Advise patients how to recognize such a reaction and when to seek medical attention [see Contraindications (4), Warnings and Precautions (5.8), Adverse Reactions (6)].

Serotonin Syndrome

Inform patients that opioids could cause a rare but potentially life-threatening condition resulting from concomitant administration of serotonergic drugs. Warn patients of the symptoms of serotonin syndrome and to seek medical attention right away if symptoms develop. Instruct patients to inform their physicians if they are taking, or plan to take serotonergic medications [see Drug Interactions (7)].

MAOI Interaction

Inform patients to avoid taking oxymorphone hydrochloride tablets while using any drugs that inhibit monoamine oxidase.

Patients should not start MAOIs while taking oxymorphone hydrochloride tablets [see Drug Interactions (7)].

Important Administration Instructions

Instruct patients how to properly take oxymorphone hydrochloride tablets exactly as prescribed to reduce the risk of life-threatening adverse reactions (e.g., respiratory depression).

- Advise patients not to adjust the dose of oxymorphone hydrochloride tablets without consulting with a physician or other healthcare professional.

Important Discontinuation Instructions

In order to avoid developing withdrawal symptoms, instruct patients not to discontinue oxymorphone hydrochloride tablets without first discussing a tapering plan with the prescriber [see Dosage and Administration (2.9)]

Driving or Operating Heavy Machinery

Inform patients that oxymorphone hydrochloride tablets may impair the ability to perform potentially hazardous activities such as driving a car or operating heavy machinery. Advise patients not to perform such tasks until they know how they will react to the medication [see Warnings and Precautions (5.15)].

Constipation

Advise patients of the potential for severe constipation, including management instructions and when to seek medical attention [see Adverse Reactions (6)].

Adrenal Insufficiency

Inform patients that opioids could cause adrenal insufficiency, a potentially life-threatening condition. Adrenal insufficiency may present with non-specific symptoms and signs such as nausea, vomiting, anorexia, fatigue, weakness, dizziness, and low blood pressure. Advise patients to seek medical attention if they experience a constellation of these symptoms [see Warnings and Precautions (5.9)].

Hypotension

Inform patients that oxymorphone hydrochloride tablets may cause orthostatic hypotension and syncope. Instruct patients how to recognize symptoms of low blood pressure and how to reduce the risk of serious consequences should hypotension occur (e.g., sit or lie down, carefully rise from a sitting or lying position) [see Warnings and Precautions (5.10)].

Pregnancy

Neonatal Opioid Withdrawal Syndrome

Inform female patients of reproductive potential that use of oxymorphone hydrochloride tablets for an extended period of time during pregnancy can result in neonatal opioid withdrawal syndrome, which may be life-threatening if not recognized and treated [see Warnings and Precautions (5.4), Use in Specific Populations (8.1)].

Embryo-Fetal Toxicity

Inform female patients of reproductive potential that oxymorphone hydrochloride tablets can cause fetal harm and to inform the healthcare provider of a known or suspected pregnancy [see Use in Specific Populations (8.1) Warnings and Precautions (5.4)].

Lactation

Advise nursing mothers to carefully observe infants for increased sleepiness (more than usual), breathing difficulties, or limpness. Instruct nursing mothers to seek immediate medical care if they notice these signs [see Use in Specific Populations (8.1)].

Infertility

Inform patients that use of opioids for an externded period of time may cause reduced fertility. It is not known whether these effects on fertility are reversible [see Adverse Reactions (6.2)].

Manufactured by:
KVK-Tech, Inc.
110 Terry Drive
Newtown, PA 18940

Item ID#: 6182/13 11/2025

Manufacturer’s Code: 10702

MEDICATION GUIDE

Oxymorphone Hydrochloride (ox'' i mor' fone hye'' droe klor' ide) Tablets, for oral use, CII

Oxymorphone hydrochloride tablets are:

- A strong prescription pain medicine that contains an opioid (narcotic) that is used to manage short-term (acute) pain when other pain treatments such as non-opioid pain medicines do not treat your pain well enough or you cannot tolerate them.
- An opioid pain medicine that can put you at risk for overdose and death. Even if you take your dose correctly as prescribed you are at risk for opioid addiction, abuse, and misuse that can lead to death.

Important information about oxymorphone hydrochloride tablets:

- Get emergency help or call 911 right away if you take too muchoxymorphone hydrochloride tablets (overdose).When you first start taking oxymorphone hydrochloride tablets, when your dose is changed, or if you take too much (overdose), serious or life-threatening breathing problems that can lead to death may occur. Ask your healthcare provider about medicines like naloxone or nalmefene that can be used in an emergency to reverse an opioid overdose.
- Taking oxymorphone hydrochloride tablets with other opioid medicines, benzodiazepines, gabapentinoids (gabapentin or pregabalin), alcohol, or other central nervous system depressants (including street drugs) can cause severe drowsiness, decreased awareness, breathing problems, coma, and death.
- Never give anyone else your oxymorphone hydrochloride tablets. They could die from taking it. Selling or giving away oxymorphone hydrochloride tablets is against the law.
- Store oxymorphone hydrochloride tablets securely, out of sight and reach of children, and in a location not accessible by others, including visitors to the home.

Do not take oxymorphone hydrochloride tablets if you have:

- severe asthma, trouble breathing, or other lung problems.
- a bowel blockage or have narrowing of the stomach or intestines.

Before taking oxymorphone hydrochloride tablets, tell your healthcare provider if you have a history of:

- head injury, seizures ● liver, kidney, thyroid problems
- problems urinating ● pancreas or gallbladder problems
- abuse of street or prescription drugs, alcohol addiction, opioid overdose or mental health problems.

Tell your healthcare provider if you are:

- Noticing your pain getting worse. If your pain gets worse after you take oxymorphone hydrochloride tablets, do not take more of oxymorphone hydrochloride tablets without first talking to your healthcare provider. Talk to your healthcare provider if the pain that you have increases, if you feel more sensitive to pain, or if you have new pain after taking oxymorphone hydrochloride tablets
- pregnant or planning to become pregnant.Use of oxymorphone hydrochloride tablets for an extended period of time during pregnancy can cause withdrawal symptoms in your newborn baby that could be life-threatening if not recognized and treated.
- breastfeeding.Oxymorphone hydrochloride tablets passes into breast milk and may harm your baby. Carefully observe infants for increased sleepiness (more than usual), breathing difficulties, or limpness. Seek immediate medical care if you notice these signs.
- living in a household where there are small children or someone who has abused street or prescription drugs.
- taking prescription or over-the-counter medicines, vitamins, or herbal supplements. Taking oxymorphone hydrochloride tablets with certain other medicines can cause serious side effects that could lead to death.

When taking oxymorphone hydrochloride tablets:

- Do not change your dose. Take oxymorphone hydrochloride tablets exactly as prescribed by your healthcare provider. Use the lowest dose possible for the shortest time needed.
- For acute (short-term) pain, you may only need to take oxymorphone hydrochloride tablets for a few days. You may have some oxymorphone hydrochloride tablets left over that you did not use. See disposal information at the bottom of this section for directions on how to safely throw away (dispose of) your unused oxymorphone hydrochloride tablets.
- Oxymorphone hydrochloride tablets should be taken on an empty stomach, at least one hour prior to or two hours after eating.
- Take your prescribed dose every 4 to 6 hours at the same time every day as needed for pain. Do not take more than your prescribed dose. If you miss a dose, take your next dose at your usual time.
- Call your healthcare provider if the dose you are taking does not control your pain.
- If you have been taking oxymorphone hydrochloride tablets regularly, do not stop taking oxymorphone hydrochloride tablets without talking to your healthcare provider.
- Dispose of remaining, unused, or expired oxymorphone hydrochloride tablets by a medicine take back program at a U.S. Drug Enforcement Administration (DEA)authorized collection site. If no takeback program or DEAauthorized collector is available, mix oxymorphone hydrochloride tablets with an undesirable, nontoxic substance such as dirt, cat litter, or used coffee grounds to make it less appealing to children and pets. Place the mixture in a container such as a sealed plastic bag and throw oxymorphone hydrochloride tablets in the household trash. Visit www.fda.gov/drugdisposalfor additional information on disposal of unused medicines.”

While taking oxymorphone hydrochloride tablets DO NOT:

- Drive or operate heavy machinery, until you know how oxymorphone hydrochloride tablets affects you. Oxymorphone hydrochloride tablets can make you sleepy, dizzy, or lightheaded.
- Drink alcohol or use prescription or over-the-counter medicines that contain alcohol. Using products containing alcohol during treatment with oxymorphone hydrochloride tablets may cause you to overdose and die.

The possible side effects of oxymorphone hydrochloride tablets:

- constipation, nausea, sleepiness, vomiting, tiredness, headache, dizziness, abdominal pain. Call your healthcare provider if you have any of these symptoms and they are severe.

Get emergency medical help or call 911 right away if you have:

- trouble breathing, shortness of breath, fast heartbeat, chest pain, swelling of your face, tongue, or throat, or hands, hives, itching, rash, extreme drowsiness, light-headedness when changing positions, feeling faint, agitation, high body temperature, trouble walking, stiff muscles, or mental changes such as confusion.

These are not all the possible side effects of oxymorphone hydrochloride tablets. Call your healthcare provider for medical advice about side effects. You may report side effects to FDA at 1-800-FDA-1088. For more information go to dailymed.nlm.nih.gov

This Medication Guide has been approved by the U.S. Food and Drug Administration.

Manufactured by:

KVK-Tech, Inc.

110 Terry Drive

Newtown, PA 18940

Item ID#: 6182/13 11/2025

Manufacturer’s Code: 10702

Package Label - Principal Display Panel – 60-Count Bottle for 5 mg Tablet

NDC 10702- 070-06

Oxymorphone Hydrochloride Tablets CII
5 mg

Pharmacist: Dispense the accompanying Medication Guide to each patient.

RX only

60 Tablets

KVK-TECH

Package Label - Principal Display Panel – 100-Count Bottle for 5 mg Tablet

NDC 10702- 070-01
Oxymorphone Hydrochloride Tablets CII
5 mg

Pharmacist: Dispense the accompanying Medication Guide to each patient.

RX only

100 Tablets

KVK-TECH

Package Label - Principal Display Panel – 60-Count Bottle for 10 mg Tablet

NDC 10702- 071-06
Oxymorphone Hydrochloride Tablets CII
10 mg

Pharmacist: Dispense the accompanying Medication Guide to eavh patient.

RX only

60 Tablets

KVK-TECH

Package Label - Principal Display Panel – 100-Count Bottle for 10 mg Tablet

NDC 10702- 071-01
Oxymorphone Hydrochloride Tablets CII
10 mg

Pharmacist: Dispense the accompanying Medication Guide to eavh patient.

RX only

100 Tablets

KVK-TECH